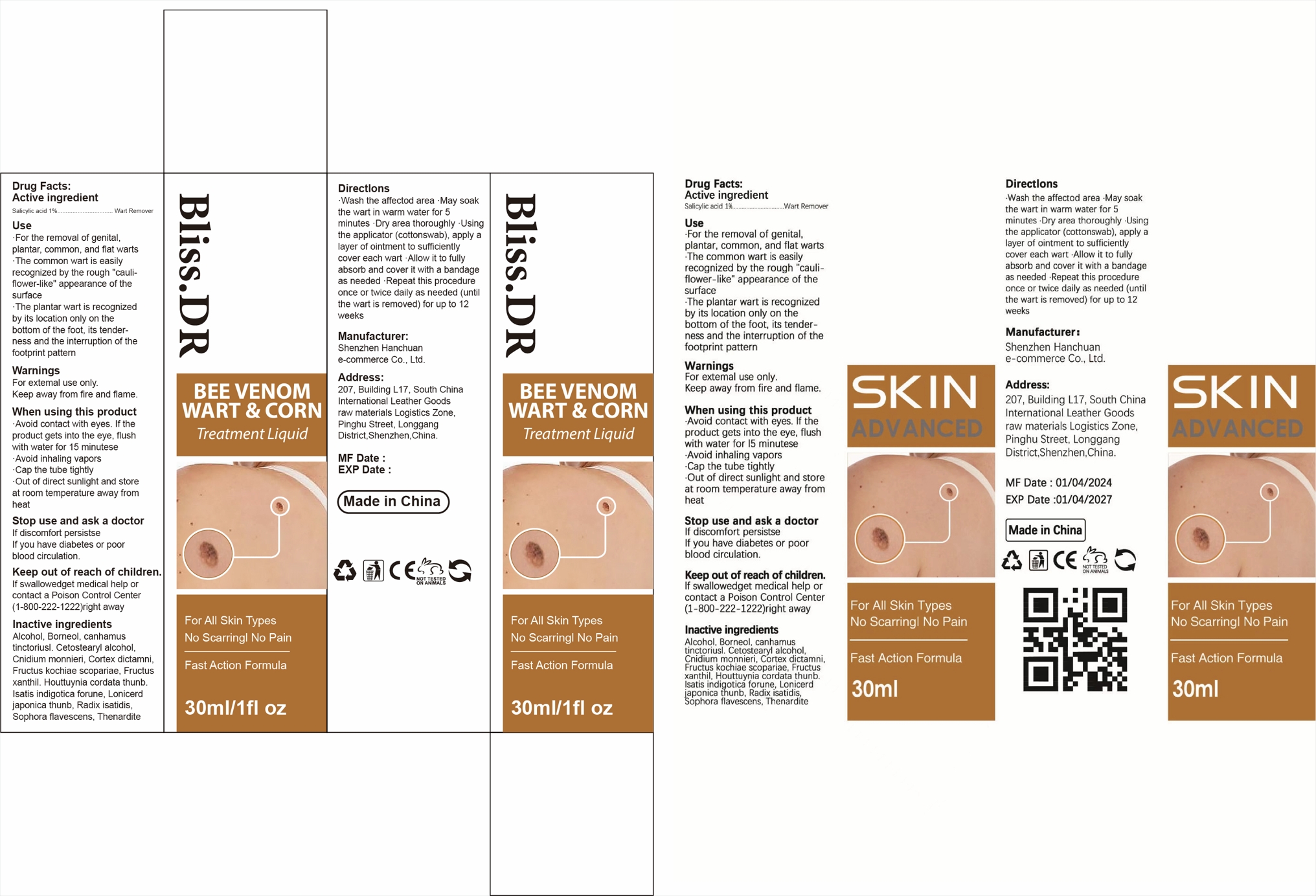 DRUG LABEL: WART REMOVER
NDC: 84302-001 | Form: LIQUID
Manufacturer: Shenzhen Hanchuan e-commerce Co., Ltd
Category: otc | Type: HUMAN OTC DRUG LABEL
Date: 20250711

ACTIVE INGREDIENTS: SALICYLIC ACID 1 g/100 mL
INACTIVE INGREDIENTS: GENTIANA SCABRA ROOT; PURSLANE; GLYCERYL GLUCOSIDE; GLYCERIN; ALCOHOL; ALOE; GLYCYRRHIZINATE DIPOTASSIUM; WATER; ERYTHRITOL; TRETINOIN; XANTHAN GUM; PHENOXYETHANOL; PROPYLENE GLYCOL; DIMETHYL ISOSORBIDE

WART REMOVER

WART REMOVER

ACTIVE INGREDIENT

Salicylic acid 1%

PURPOSE

Wart Remover

INDICATIONS AND USAGE

For the removal of genital,plantar, common, and flat warts.
The common wart is easilyrecognized by the rough "cauli-flower-like" appearance of thesurface.
The plantar wart is recognizedby its location only on thebottom of the foot, its tender-ness and the interruption of thefootprint pattern.

WARNINGS

For extemal use only.

Keep away from fire and flame.

WHEN USING

Avoid contact with eyes. If theproduct gets into the eye, flushwith water for 15 minutese.
Avoid inhaling vapors.
Cap the tube tightly.
Out of direct sunlight and storeat room temperature away fromheat.

STOP USE

lf discomfort persistself you have diabetes or poor blood circulation.

KEEP OUT OF REACH OF CHILDREN

If swallowedget medical help orcontact a Poison Control Center(1-800-222-1222)right away

DOSAGE AND ADMINISTRATION

.Wash the affectod area May soakthe wart in warm water for 5minutes Dry area thoroughly Usingthe applicator (cottonswab), apply alayer of ointment to sufficientlycover each wart ·Allow it to fullyabsorb and cover it with a bandageas needed Repeat this procedureonce or twice daily as needed (untilthe wart is removed) for up to 12weeks

STORAGE AND HANDLING

Out of direct sunlight and storeat room temperature away fromheat.

INACTIVE INGREDIENT

Water
Alcohol
Glycerin
Propylene Glycol
Dimethyl Isosorbide
Erythritol
Phenoxyethanol
Aloe Yohjyu Matsu Ekisu
Glyceryl Glucoside
Portulaca Oleracea Extract
Gentiana Scabra Root Extract
Xanthan Gum
Retinoic Acid
Dipotassium Glycyrrhizate